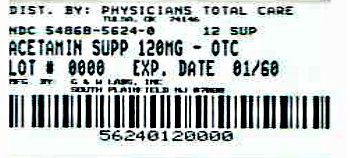 DRUG LABEL: Acetaminophen
NDC: 54868-5624 | Form: SUPPOSITORY
Manufacturer: Physicians Total Care, Inc.
Category: otc | Type: HUMAN OTC DRUG LABEL
Date: 20120606

ACTIVE INGREDIENTS: Acetaminophen 120 mg/1 1
INACTIVE INGREDIENTS: Butylated Hydroxyanisole; Butylated Hydroxytoluene; Glyceryl Monostearate; Hydrogenated Coconut Oil; Peg-100 Stearate; Polysorbate 80

Pediatric AcephenTM, Acetaminophen Suppositories, 120 mg

ACTIVE INGREDIENT (in each rectal suppository)

Acetaminophen 120 mg

PURPOSE

pain reliever/fever reducer

USES

temporarily
• reduces fever
• relieves minor aches, pains, and headache

WARNINGS

For rectal use only
Liver Warning: This product contains acetaminophen. Severe liver damage may occur if your child inserts:
• more than 5 suppositories in 24 hours, which is the maximum daily amount
• with other drugs containing acetaminophen
Do not use
• if your child is allergic to acetaminophen
• with any other drug containing acetaminophen (prescription or nonprescription). If you are not sure whether a drug contains acetaminophen, ask a doctor or pharmacist.
Ask a doctor before use if your child has liver disease
Ask a doctor or pharmacist before use if your child is taking the blood thinning drug warfarin
Stop use and ask a doctor if
• fever lasts more than 3 days (72 hours), or recurs
• you need to use this product for pain for more than 5 days continuously
Severe or recurrent pain, or high or continued fever may indicate a serious illness.

KEEP OUT OF REACH OF CHILDREN

If swallowed or in case of overdose, get medical help or contact a Poison Control Center right away. Quick medical attention is critical in case of overdose for children even if you do not notice any signs or symptoms.

DOSAGE & ADMINISTRATION

Directions
This product does not contain directions or complete warnings for adult use.
• do not use more than directed
• remove foil wrapper
• insert suppository well up into rectum
• children 3-6 years:
• 1 suppository every 4 to 6 hours while symptoms persist
• do not exceed 5 suppositories in any 24-hour period
• children under 3 years: ask a doctor

Other Information

• for your safety, suppositories are packaged in tamper-evident sealed foil. Do not use if foil is torn or open.
• store at 8˚-25˚C (46˚-77˚F)

INACTIVE INGREDIENT

butylated hydroxyanisole, butylated hydroxytoluene, glyceryl stearate, hydrogenated vegetable oil, polyethylene glycol 100 stearate, polysorbate 80

QUESTIONS

call 1-800-922-1038
Monday-Friday 9am-4pm EST

PACKAGE LABEL.PRINCIPAL DISPLAY PANEL

SEE NEW WARNINGS INFORMATION
READ AND KEEP CARTON FOR NEW LIVER WARNING
NDC 54868-5624-0
12 rectal suppositories
Acetaminophen Suppositories USP 120 mg
ASPIRIN FREE
Pain Reliever • Fever Reducer
50 Rectal Suppositories